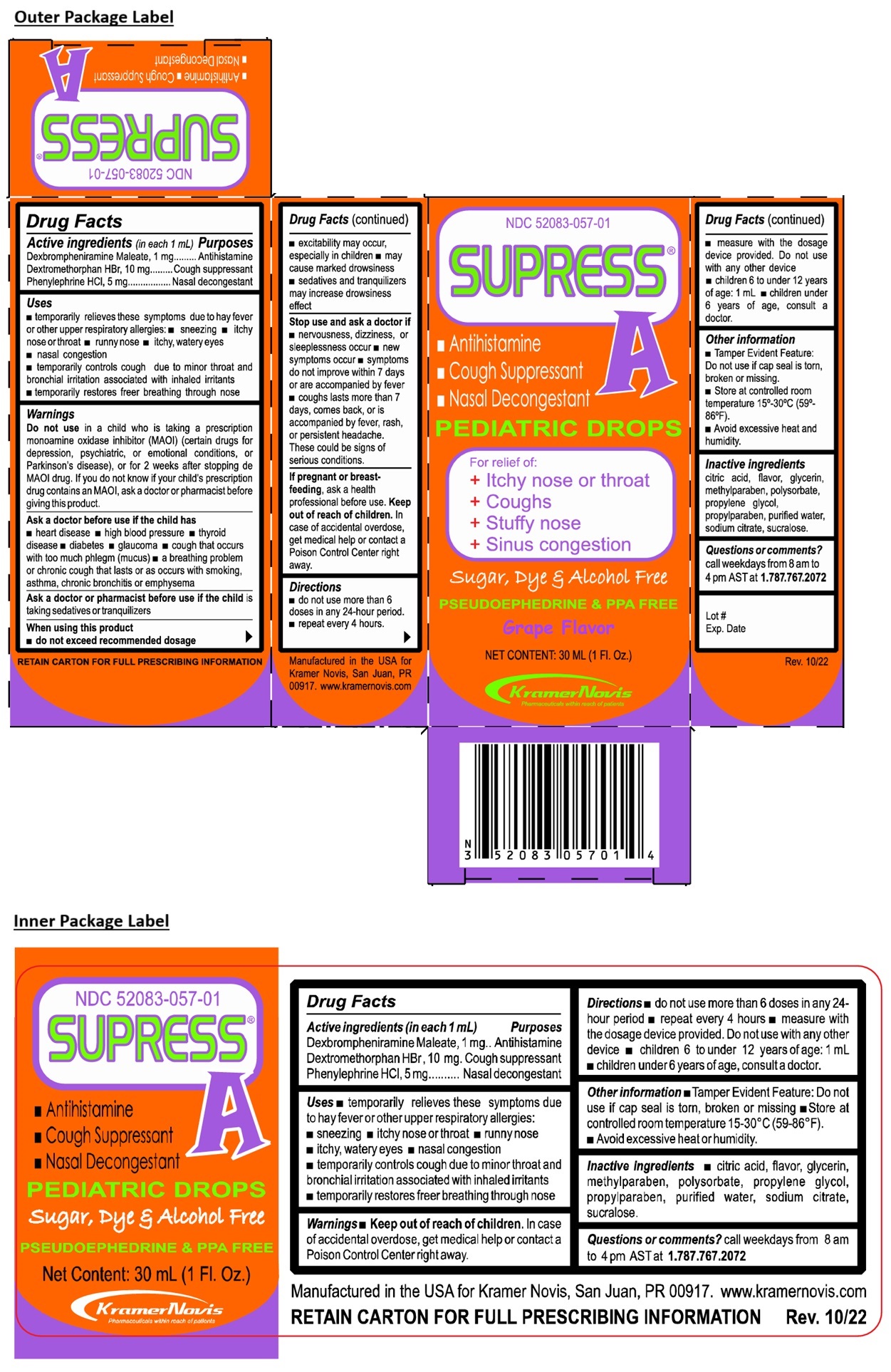 DRUG LABEL: SUPRESS A
NDC: 52083-057 | Form: SYRUP
Manufacturer: Kramer Novis
Category: otc | Type: HUMAN OTC DRUG LABEL
Date: 20250922

ACTIVE INGREDIENTS: DEXBROMPHENIRAMINE MALEATE 1 mg/1 mL; DEXTROMETHORPHAN HYDROBROMIDE 10 mg/1 mL; PHENYLEPHRINE HYDROCHLORIDE 5 mg/1 mL
INACTIVE INGREDIENTS: CITRIC ACID MONOHYDRATE; GLYCERIN; METHYLPARABEN; POLYSORBATE 20; PROPYLENE GLYCOL; PROPYLPARABEN; WATER; SODIUM CITRATE; SUCRALOSE

SUPRESS A

Active ingredients (in each 1 mL)

Dexbrompheniramine Maleate, 1 mg

Dextromethorphan HBr, 10 mg

Phenylephrine HCl, 5 mg

Purposes

Antihistamine

Cough suppressant

Nasal decongestant

Uses

• temporarily relieves these symptoms due to hay fever or other upper respiratory allergies: • sneezing • itchy nose or throat • runny nose • itchy, watery eyes
• nasal congestion
• temporarily controls cough due to minor throat and bronchial irritation associated with inhaled irritants
• temporarily restores freer breathing through nose

Warnings

Do not use in a child who is taking a prescription monoamine oxidase inhibitor (MAOI) (certain drugs for depression, psychiatric or emotional conditions, or Parkinson’s disease), or for 2 weeks after stopping the MAOI drug. If you do not know if your child's prescription drug contains an MAOI, ask a doctor or pharmacist before giving this product.

Ask a doctor before use if the child has
• heart disease • high blood pressure • thyroid disease • diabetes • glaucoma • cough that occurs with too much phlegm (mucus) • a breathing problem or chronic cough that lasts or as occurs with smoking, asthma, chronic bronchitis, or emphysema

Ask a doctor or pharmacist before use if the child is taking sedatives or tranquilizers

When using this product
• do not exceed recommended dosage
• excitability may occur, especially in children • may cause marked drowsiness • sedatives and tranquilizers may increase drowsiness effect

Stop use and ask a doctor if • nervousness, dizziness, or sleeplessness occur • new symptoms occur • symptoms do not improve within 7 days or are accompanied by fever • cough lasts more than 7 days, comes back, or is accompanied by fever, rash, or persistent headache.
These could be signs of a serious condition.

If pregnant or breast-feeding, ask a health professional before use.

Keep out of reach of children. In case of accidental overdose, get medical help or contact a Poison Control Center right away.

Directions

• do not use more than 6 doses in any 24-hour period.
• repeat every 4 hours.
• measure with the dosage device provided. Do not use with any other device
• children 6 to under 12 years of age: 1 mL • children under 6 years of age, consult a docotor.

Other information

- Tamper Evident Feature: Do not use if cap seal is torn, broken or missing.
- Store at controlled room temperature 15°-30°C (59° to 86°F).
- Avoid excessive heat and humidity.

Inactive ingredients

Citric acid, flavor, glycerin, methylparaben, polysorbate, propylene glycol, propylparaben, purified water, sodium citrate, sucralose.

Questions or comments?

call weekdays from 8 am to 4 pm AST at 1.787.767.2072

For relief of:
+ Itchy nose or throat
+ Coughs
+ Stuffy nose
+ Sinus congestion

Sugar, Dye & Alcohol Free

PSEUDOEPHEDRINE & PPA FREE

RETAIN CARTON FOR FULL PRESCRIBING INFORMATION

Manufactured in the USA for Kramer Novis, San Juan, PR 00917. www.kramernovis.com